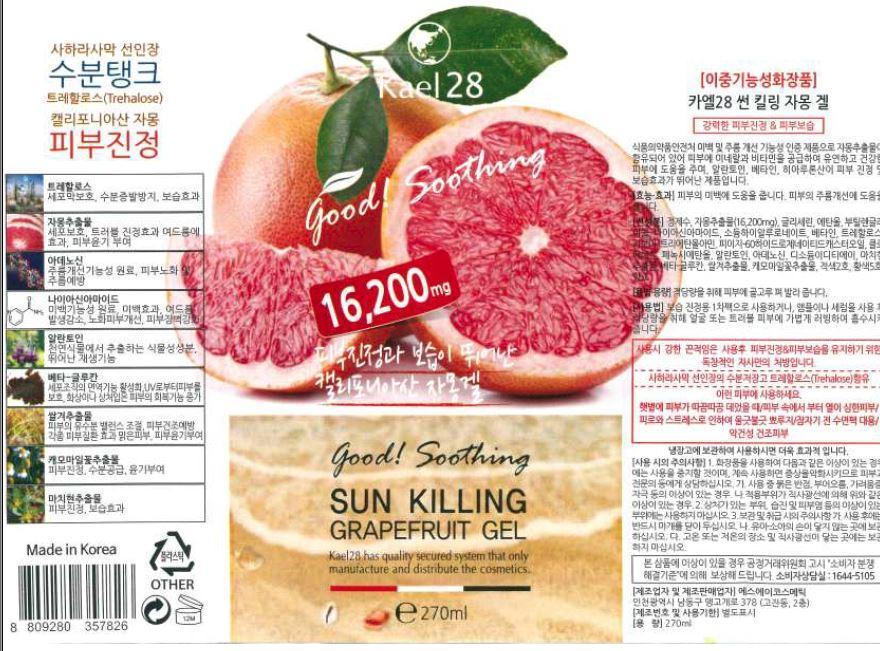 DRUG LABEL: SUN KILLING GRAPEFRUIT
NDC: 69663-1001 | Form: GEL
Manufacturer: SA Cosmetic
Category: otc | Type: HUMAN OTC DRUG LABEL
Date: 20150314

ACTIVE INGREDIENTS: GLYCERIN 5 g/100 mL
INACTIVE INGREDIENTS: WATER; BUTYLENE GLYCOL; ALLANTOIN

Drug Facts

ACTIVE INGREDIENT

glycerine

INACTIVE INGREDIENT

water, alcohol, butylene glycol, betain, carbomer, adenosine, beta glucan, etc

PURPOSE

skin protectant

skin soothing

keep out of reach of the children

INDICATIONS AND USAGE

use as primary pack for moisturizing relief by applying on skin after using ampoule or serum
gently massage for absorption

WARNINGS

・Stop using the product when you have skin problems or the product disagrees with your skin
・Stop using the product immediately and consult a dermatologist if you have redness, swelling, itching or irritation on the skin while or after using the product.
・Don't place the product in any place where it will be subjected to extremely high or low temperatures or direct sunlight.

DOSAGE AND ADMINISTRATION

for external use only